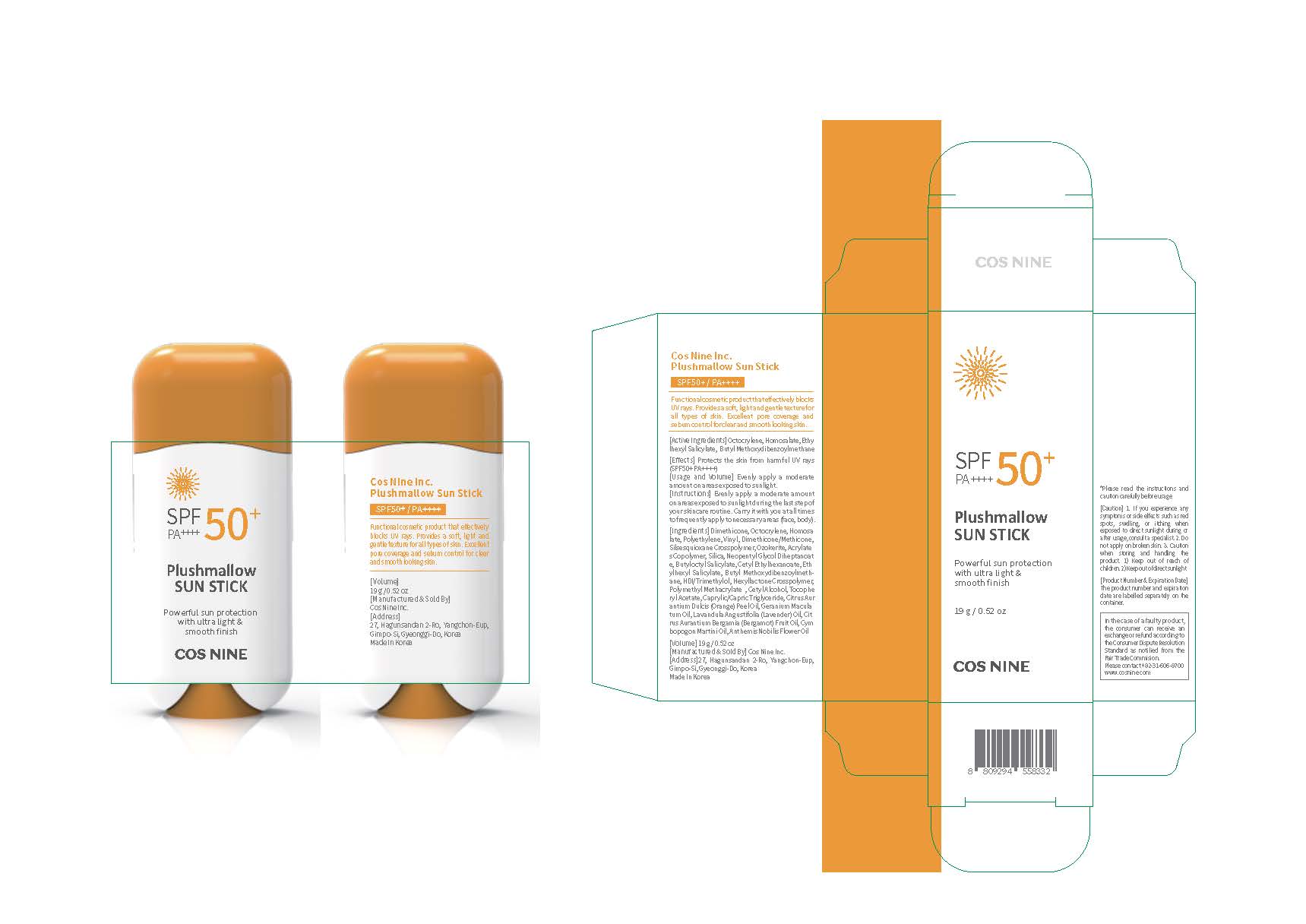 DRUG LABEL: Plushmallow SUNSTICK
NDC: 73330-0001 | Form: STICK
Manufacturer: COSNINE Inc
Category: otc | Type: HUMAN OTC DRUG LABEL
Date: 20190831

ACTIVE INGREDIENTS: OCTOCRYLENE 9.5 g/100 g; AVOBENZONE 3 g/100 g; HOMOSALATE 9.5 g/100 g; OCTISALATE 4.5 g/100 g
INACTIVE INGREDIENTS: DIMETHICONE

Drug Facts

ACTIVE INGREDIENT

Octocrylene, Homosalate, Ethylhexyl Salicylate, Butyl Methoxydibenzoylmethane

INACTIVE INGREDIENT

Dimethicone
Polyethylene
Vinyl Dimethicone/Methicone Silsesquioxane Crosspolymer
Ozokerite
Acrylates Copolymer
Silica
Neopentyl Glycol Diheptanoate
Butyloctyl Salicylate
Cetyl Ethylhexanoate
HDI/Trimethylol Hexyllactone Crosspolymer
Polymethyl Methacrylate
Cetyl Alcohol
Tocopheryl Acetate
Caprylic/Capric Triglyceride
Citrus Aurantium Dulcis (Orange) Peel Oil
Geranium Maculatum Oil
Lavandula Angustifolia (Lavender) Oil
Citrus Aurantium Bergamia (Bergamot) Fruit Oil
Cymbopogon Martini Oil
Anthemis Nobilis Flower Oil

PURPOSE

protects the skin from harmful UV rays (SPF50+ PA++++)

keep out of reach of the children

INDICATIONS AND USAGE

Evenly apply a moderate amount
on areas exposed to sunlight during the last step of
your skincare routine. Carry it with you at all times
to frequently apply to necessary areas (face, body).

WARNINGS

1. While using this product , if there
is any abnormal symptoms or side effect such as red spot,
swelling or itching, please consult with dermatologist.
2. Do not use in areas with wounds 3. Instructions for sto
-rage and usage. (i) Keep out of reach of infants and chil
-dren (ii) Store it in a place away from direct sunlight

DOSAGE AND ADMINISTRATION

for external use only